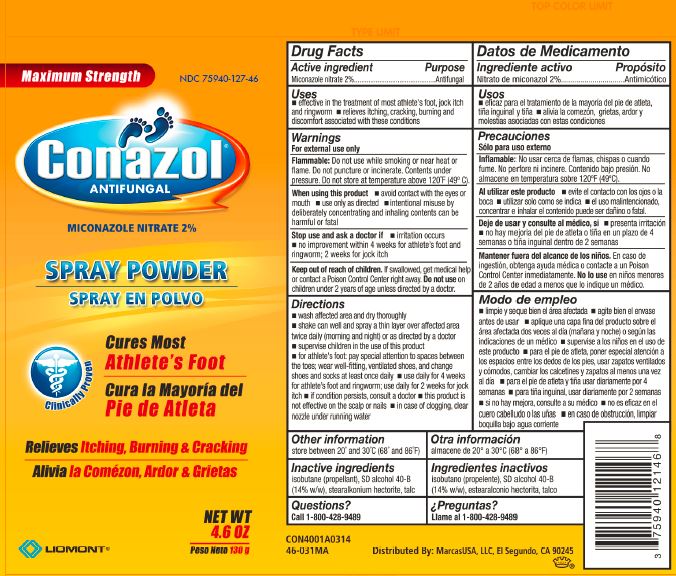 DRUG LABEL: Conazol
NDC: 75940-127 | Form: SPRAY
Manufacturer: MarcasUSA LLC
Category: otc | Type: HUMAN OTC DRUG LABEL
Date: 20200127

ACTIVE INGREDIENTS: MICONAZOLE NITRATE 20 mg/1 g
INACTIVE INGREDIENTS: ISOBUTANE; ALCOHOL; STEARALKONIUM HECTORITE; TALC

Conazol Spray Powder

Active Ingredients Purpose

Active ingredients
Miconazole nitrate 2%

Purpose
Antifungal

INDICATIONS AND USAGE

Uses

- effective in the treatment of most athlete's foot, jock
  itch and ringworm
- relieves itching, cracking, burning and discomfort
  associated with these conditions

Warnings

For external use only

Flammable: Do not use while smoking or near heat or flame. Do not puncture or incinerate. Contents under pressure. Do not store at temperature above 120°F (49°C).

When using this product

- avoid contact with the eyes or mouth
- use only as directed
- intentional misuse by deliberately concentrating and inhaling contents can be harmful or fatal

Stop use and ask a doctor if

- irritation occurs
- no improvement within 4 weeks for athlete's foot and ringworm; 2 weeks for jock itch

Keep out of reach of children

If swallowed, get medical help or contact a Poison Control Center right away. Do not use on children under 2 years of age unless directed by a doctor.

Directions

- wash affected area and dry thoroughly
- shake can well and spray a thin layer over affected area twice daily (morning and night) or as directed by a doctor
- supervise children in the use of this product
- for athlete's foot, pay special attention to the spaces between the toes; wear well-fitting, ventilated shoes, and change shoes and socks at least once daily
- use daily for 4 weeks for athlete's foot and ringworm; use daily for 2 weeks for jock itch
- if condition persists, consult a doctor
- this product is not effective on the scalp or nails
- in case of clogging, clear nozzle under running water

Other Information

store between 20° and 30°C (68° and 86°F)

Inactive Ingredients

isobutane (propellant), SD alcohol 40-B (14% w/w), stearalkonium hectorite, talc

Questions?

Call Toll-Free 1-800-428-9489

Distributed By: MarcasUSA, LLC, El Segundo, CA 90245

Datos de Medicamento

ACTIVE INGREDIENT

Ingrediente Activo
Nitrato de miconazol 2%

Propósito
Antimicótico

Usos

- eficaz para el tratamiento de la mayoría del pie de atleta, tiña inguinal y tiña
- alivia la comezón, grietas, ardor y molestias asociadas con estas condiciones

Precauciones

Sólo para uso externo

lnflamable: No usar cerca de flamas, chispas o cuando fume. No perfore ni incinere. Contenido bajo presión. No almacene en temperatura sobre 120°F (49°C).

Al utilizar este producto

- evite el contacto con los ojos o la boca
- utilizar solo como se indica
- el uso malintencionado, concentrar e inhalar el contenido puede ser dañino o fatal.

Deje de usar y consulte al médico, si

- presenta irritación
- no hay mejoria del pie de atleta o tiña en un plazo de 4 semanas o tiña inguinal dentro de 2 semanas

Mantener fuera del alcance de los niños.

En caso de ingestión, obtenga ayuda médica o contacte a un Poison Control Center inmediatamente. No lo use en niños menores de 2 años de edad a menos que lo indique un médico.

Modo de empleo

- limpie y seque bien el área afectada
- agite bien el envase antes de usar
- aplique una capa fina del producto sobre el área afectada dos veces al día (mañana y noche) o según las indicaciones de un médico
- supervise a los niños en el uso de este producto
- para el pie de atleta, poner especial atención a los espacios entre los dedos de los pies, usar zapatos ventilados y cómodos, cambiar los calcetines y zapatos al menos una vez al día
- para el pie de atleta y tiña usar diariamente por 4 semanas
- para tiña inguinal, usar diariamente por 2 semanas
- si no hay mejora, consulte a su médico
- no es eficaz en el cuero cabelludo o las uñas
- en caso de obstrucción, limpiar boquilla bajo agua corriente

Otra información

almacene de 20° a 30°C (68° a 86° F)

Ingredientes Anactivos

isobutano (propelente), SD alcohol 40-B (14% w/w), estearalconio hectorita, talco

¿Preguntas?

Llame al 1-800-428-9489

Distributed By: MarcasUSA, LLC, El Segundo, CA 90245

PACKAGE LABEL.PRINCIPAL DISPLAY PANEL

Maximum Strength NDC 75940-127-46

Conazol
Antifungal

MICONAZOLE NITRATE 2%

SPRAY POWDER
SPRAY EN POLVO

Cures Most
Athlete's Foot

Cura la Mayoría del
Pie de Atleta

Relieves Itching, Burning & Cracking

Alivia la Comézon, Ardor & Grietas

LIOMONT

NET WT
4.6 OZ
Peso Neto 130 g